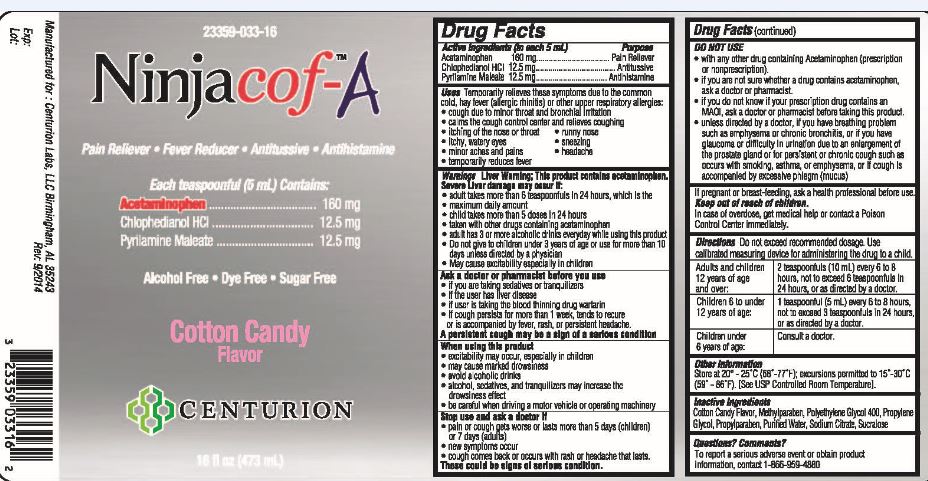 DRUG LABEL: Ninjacof-A 
NDC: 23359-033 | Form: LIQUID
Manufacturer: Centurion Labs, LLC
Category: otc | Type: HUMAN OTC DRUG LABEL
Date: 20141120

ACTIVE INGREDIENTS: Acetaminophen 160 mg/5 mL; Chlophedianol Hydrochloride 12.5 mg/5 mL; Pyrilamine Maleate 12.5 mg/5 mL
INACTIVE INGREDIENTS: Methylparaben; Polyethylene Glycol 400; Propylene Glycol; Propylparaben; Water; Sodium Citrate; Sucralose

Active Ingredients (in each 5 mL) | Purposes
Acetaminophen 160 mg | Pain Reliever
Chlophedianol HCl 12.5 mg | Antitussive
Pyrilamine Maleate 12.5mg | Antihistamine

Uses

Temporarily relieves these symptoms due to the common cold, hay fever (allergic rhinitis) or other upper respiratory allergies:

- cough due to minor throat and bronchial irritation
- calms the cough control center and relieves coughing
- itching of the nose or throat
- itchy, watery eyes
- minor aches and pains
- temporarily reduces fever
- runny nose
- sneezing
- headache

Warnings

Liver Warning; This product contains acetaminophen. Severe Liver damage may occur if:

- adult takes more than 6 teaspoonfuls in 24 hours, which is the maximum daily amount
- child takes more than 5 doses in 24 hours
- taken with other drugs containing acetaminophen
- adult has 3 or more alcoholic drinks everyday while using this product
- Do not give to children under 3 years of age or use for more than 10 days unless directed by a physician
- May cause excitability especially in children

Ask a doctor or pharmacist before you use

- if you are taking sedatives or tranquilizers
- if the user has liver disease
- if user is taking the blood thinning drug warfarin
- if cough persists for more than 1 week, tends to recur or is accompanied by fever, rash, or persistent headache.

A persistent cough may be a sign of a serious condition

When using this product

- excitability may occur, especially in children
- may cause marked drowsiness
- avoid alcoholic drinks
- alcohol, sedatives, and tranquilizers may increase the drowsiness effect
- be careful when driving a motor vehicle or operating machinery

Stop use and ask a doctor if

- pain or cough gets worse or lasts more than 5 days (children) or 7 days (adults)
- new symptoms occur
- cough comes back or occurs with rash or headache that lasts.

These could be signs of serious condition.

DO NOT USE

- with any other drug containing Acetaminophen (perscription or nonprescription).
- if you are not sure whether a drug contains acetaminophen, ask a doctor or pharmacist.
- if you do not know if your prescription contains an MAOI, ask a doctor or pharmacist before taking this product.
- unless directed by a doctor, if you have breathing problems such as emphysema or chronic bronchitis, or if you have glaucoma or difficulty in urination due to an enlargement of the prostate gland or for persistent or chronic cough such as occcurs with smoking, asthma, or emphysema, or if cough is accompanied by excessive phlegm (mucus)

If pregnant or breast-feeding, ask a health professional before use.
Keep out of reach of children.
In case of overdose, get medical help or contact Poison Control Center immediately.

TERATOGENIC EFFECTS

Directions Do not exceed recommended dosage. Use calibrated measuring device for administering the drug to a child.

Adults and children 12 years of age and over: | 2 teaspoonfuls (10mL) every 6 to 8 hours, not to exceed 6 teaspoonfuls in 24 hours, or as directed by a doctor.
Children 6 to under 12 years of age: | 1 teaspoonful (5mL) every 6 to 8 hours, not to exceed 3 teaspoonfuls in 24 hours, or as directed by a doctor.
Children under 6 years of age: | Consult a doctor

Other Information

Store at 20° - 25°C (68°-77°F); excursions permitted to 15°- 30°C (59°- 86°F). [See USP Controlled Room Temperature].

Inactive Ingredients

Cotton Candy Flavor, Methylparaben, Polyethlyene Glycol 400, Propylene Glycol, Propylparaben, Purified Water, Sodium Citrate, Sucralose

Questions? Comments?

To report a serious adverse event or obtain product information, contact 1-866-959-4880

PRINCIPAL DISPLAY PANEL

23359-033-16

NinjacofTM-A

Pain Reliever • Fever Reducer • Antitussive • Anithistamine

Each teaspoonful (5mL) Contains:

Acetaminophen...........................160mg
Chlophedianol HCI.....................12.5mg
Pyrilamine Maleate.....................12.5mg

Alcohol Free • Dye Free • Sugar Free

Cotton Candy
Flavor

CENTURION

16 fl oz (473 mL)